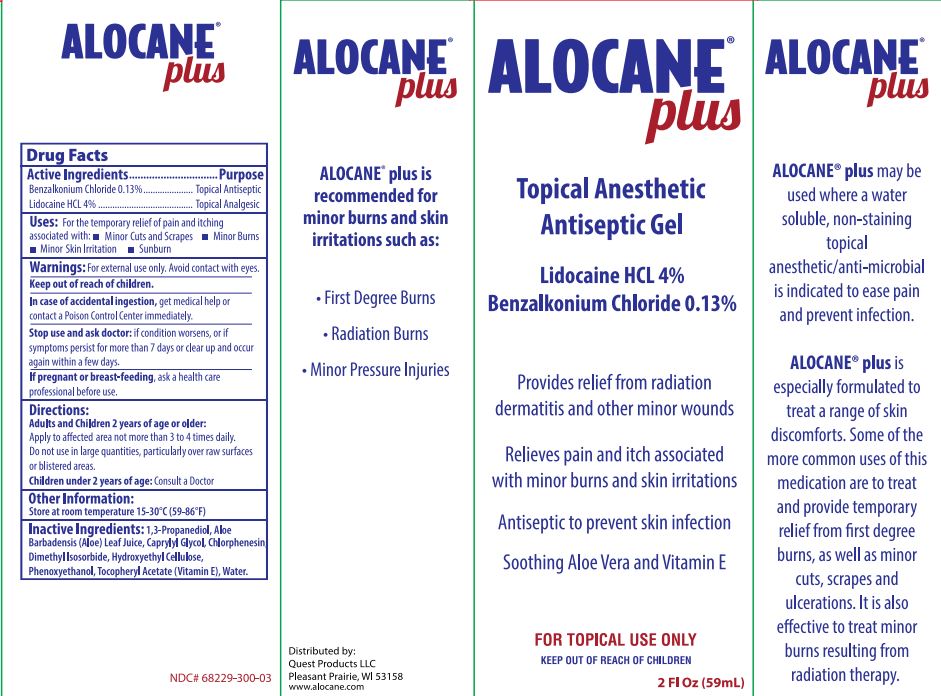 DRUG LABEL: Alocane Plus
NDC: 68229-300 | Form: GEL
Manufacturer: Quest Products, Inc.
Category: otc | Type: HUMAN OTC DRUG LABEL
Date: 20250717

ACTIVE INGREDIENTS: LIDOCAINE HYDROCHLORIDE 4 g/100 mL; BENZALKONIUM CHLORIDE 0.13 g/100 mL
INACTIVE INGREDIENTS: PROPANEDIOL; ALOE VERA LEAF; DIMETHYL ISOSORBIDE; HYDROXYETHYL CELLULOSE (5500 MPA.S AT 2%); PHENOXYETHANOL; CAPRYLYL GLYCOL; CHLORPHENESIN; .ALPHA.-TOCOPHEROL ACETATE; WATER

Alocane® Plus

Drug Facts

ACTIVE INGREDIENT

Active Ingredient | Purpose
Lidocaine HCL 4% | Topical Analgesic
Benzalkonium Chloride 0.13% | Topical Antiseptic

Uses

For the temporary relief of pain and itching associated with: Sunburn, Minor Cuts & Scrapes, Minor Skin Irritation, Minor Burns

Warnings

For external use only. Avoid contact with eyes.

Keep out of reach of children.

Stop use and ask doctor: if condition worsens, or if symptoms persist for more than 7 days or clear up and occur again within a few days.

PREGNANCY OR BREAST FEEDING

If pregnant or breast-feeding, ask a health care professional before use.

Directions

Directions

Apply to affected area not more than 3 to 4 times daily. Do not use in large quantities, particularly over raw surfaces or blistered areas.

Children under 2 years of age, consult a physician.

Other Information

Store at Room Temperature of 15° - 30°C (59° - 86°F)

Inactive Ingredients

1,3-Propanediol, Aloe Barbadensis (Aloe) Leaf Juice, Caprylyl Glycol, Chlorphenesin, Dimethyl Isosorbide, Hydroxyethyl Cellulose, Phenoxyethanol, Tocopheryl Acetate (Vitamin E), Water.

DISTRIBUTED BY
QUEST PRODUCTS LLC
Pleasant Prairie, WI 53158